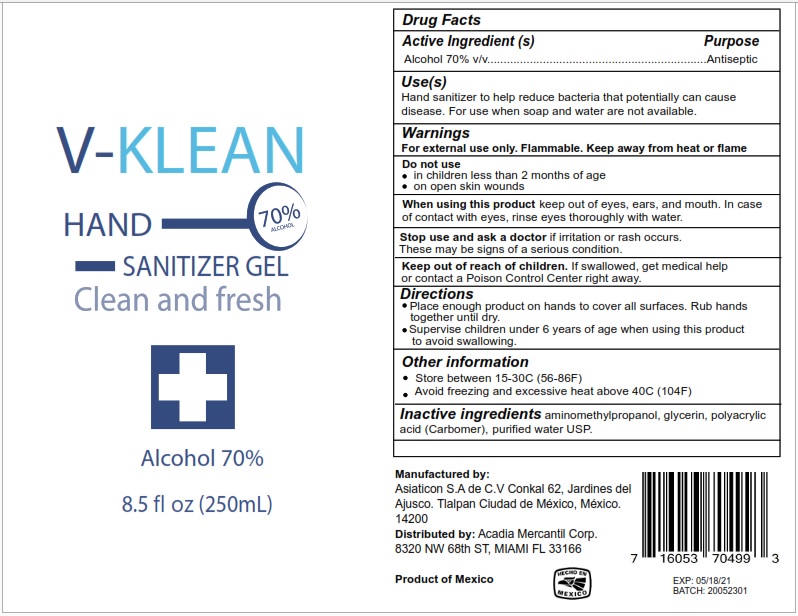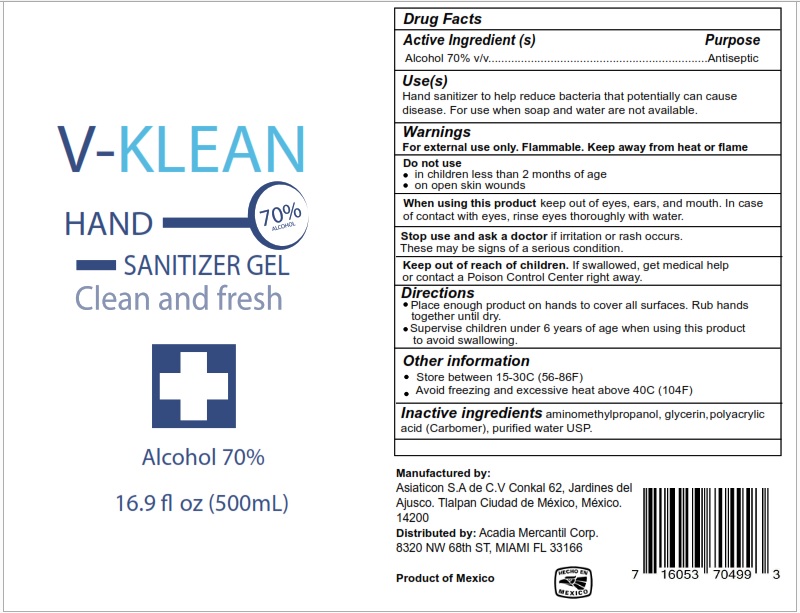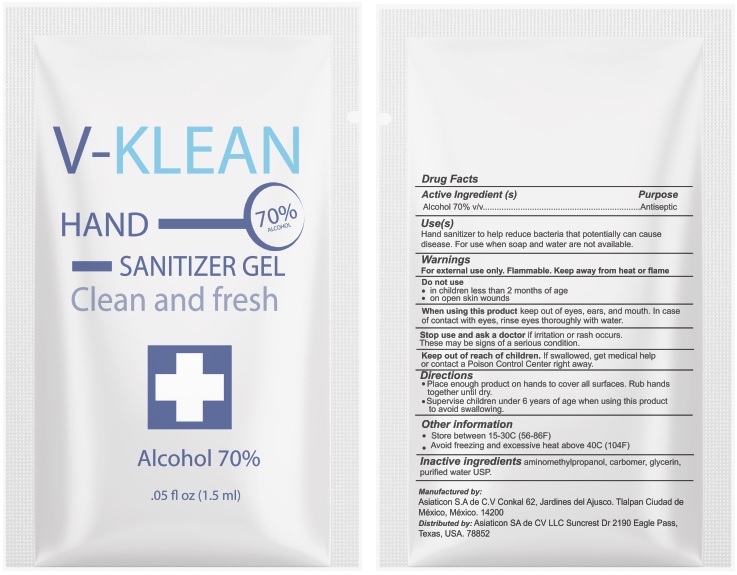 DRUG LABEL: V-KLEAN
NDC: 75192-002 | Form: GEL
Manufacturer: Asiaticon, S.A. de C.V.
Category: otc | Type: HUMAN OTC DRUG LABEL
Date: 20200820

ACTIVE INGREDIENTS: ALCOHOL 70 mL/100 mL
INACTIVE INGREDIENTS: AMINOMETHYLPROPANOL 0.5 mL/100 mL; POLYACRYLIC ACID (8000 MW) 0.3 mL/100 mL; WATER 28.35 mL/100 mL; GLYCERIN 0.85 mL/100 mL

Directions

Place enough product on hands to cover all surfaces. Rub hands together until dry.

Supervise children under 6 years of age when using this product to avoid swallowing.

Warnings

Flammable, keep away from fire and flames

For external use only

Inactive ingredients

Aminomethylpropanol, glycerin, polyacrylic acidc (Carbomer), purified water USP.

Use

Hand sanitizer for hand-washing to decrease bacteria on the skin, only when water is not available

Keep out of reach of children. If swallowed, get medical help or contact a Poison Control Center right away.

Purpose

Antiseptic, Hand sanitizer

Active Ingredient(s)

Alcohol 70% Purpose: Antiseptic

PACKAGE LABEL

250 mL NDC: 75192-002-01

Package Label - Principal Display Panel

500 mL NDC: 75192-002-02

Package Label - Principal Display Panel

1.5 mL NDC: 75192-002-04